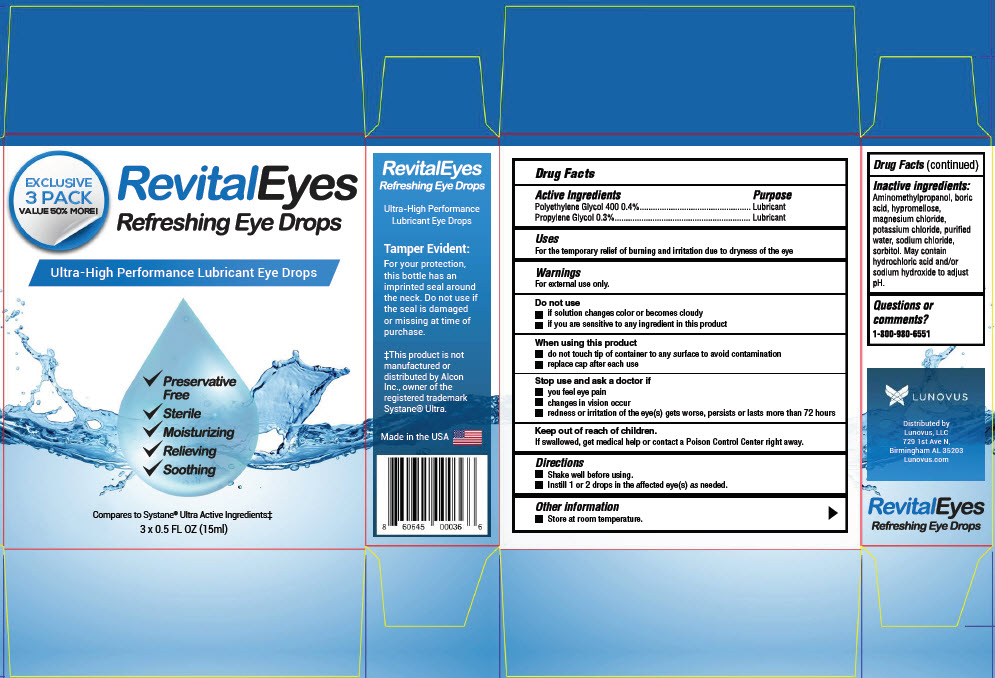 DRUG LABEL: Revital eyes
NDC: 73197-001 | Form: SOLUTION/ DROPS
Manufacturer: Lunovus, LLC
Category: otc | Type: HUMAN OTC DRUG LABEL
Date: 20190828

ACTIVE INGREDIENTS: Polyethylene Glycol 400 4 mg/1 mL; Propylene Glycol 3 mg/1 mL
INACTIVE INGREDIENTS: Aminomethylpropanol; Boric Acid; Hypromellose, Unspecified; Magnesium Chloride; Potassium Chloride; Water; Sodium Chloride; Sorbitol; Hydrochloric Acid; Sodium Hydroxide

Revital eyes

Drug Facts

ACTIVE INGREDIENT

Active Ingredients | Purpose
Polyethylene Glycol 400 0.4% | Lubricant
Propylene Glycol 0.3% | Lubricant

Uses

For the temporary relief of burning and irritation due to dryness of the eye

Warnings

For external use only.

Do not use

- if solution changes color or becomes cloudy
- if you are sensitive to any ingredient in this product

When using this product

- do not touch tip of container to any surface to avoid contamination
- replace cap after each use

Stop use and ask a doctor if

- you feel eye pain
- changes in vision occur
- redness or irritation of the eye(s) gets worse, persists or lasts more than 72 hours

Keep out of reach of children.
If swallowed, get medical help or contact a Poison Control Center right away.

Directions

- Shake well before using.
- Instill 1 or 2 drops in the affected eye(s) as needed.

Other information

- Store at room temperature.

Inactive ingredients

Aminomethylpropanol, boric acid, hypromellose, magnesium chloride, potassium chloride, purified water, sodium chloride, sorbitol. May contain hydrochloric acid and/or sodium hydroxide to adjust pH.

Questions or comments?

1-800-980-6551

Distributed by
Lunovus, LLC
729 1st Ave N,
Birmingham AL 35203

PRINCIPAL DISPLAY PANEL - 15 ml Bottle Carton

EXCLUSIVE
3 PACK
VALUE 50% MORE!

RevitalEyes
Refreshing Eye Drops

Ultra-High Performance Lubricant Eye Drops

✓ Preservative
  Free
✓ Sterile
✓ Moisturizing
✓ Relieving
✓ Soothing

Compares to Systane® Ultra Active Ingredients‡
3 x 0.5 FL OZ (15ml)